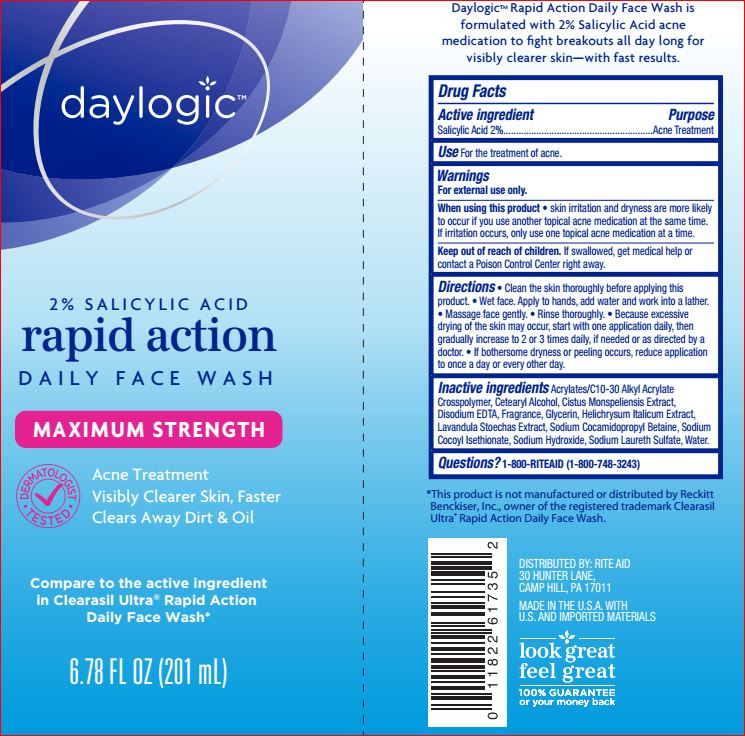 DRUG LABEL: Rapid Action Daily Face Wash
NDC: 11822-7802 | Form: CREAM
Manufacturer: Rite Aid
Category: otc | Type: HUMAN OTC DRUG LABEL
Date: 20180607

ACTIVE INGREDIENTS: Salicylic Acid 2 g/100 mL
INACTIVE INGREDIENTS: WATER; Sodium Cocoyl Isethionate; CETOSTEARYL ALCOHOL; Glycerin; Sodium Laureth Sulfate; Sodium Hydroxide; CARBOMER INTERPOLYMER TYPE A (ALLYL SUCROSE CROSSLINKED); EDETATE DISODIUM; LAVANDULA STOECHAS FLOWERING TOP; HELICHRYSUM ITALICUM FLOWER

Drug Facts

Active ingredient Purpose
Salicylic Acid 2%.........................................Acne Treatment

INDICATIONS AND USAGE

Use For the treatment of acne.

Warnings For external use only.

When using this product • skin irritation and dryness are more likely to occur if you use another topical acne medication at the same time. If irritation occurs, only use one topical acne medication at a time.

Keep out of reach of children. If swallowed, get medical help or contact a Poison Control Center right away.

DOSAGE AND ADMINISTRATION

Directions • Cleanse twice a day. • Wet face. Apply to hands, add water and work into a lather. • Massage face gently. • Rinse thoroughly.

Inactive ingredients
Acrylates/C10-30 Alkyl Acrylate Crosspolymer
Cetearyl Alcohol
Cistus Monspeliensis Extract
Disodium EDTA
Fragrance
Glycerin
Helichrysum Italicum Extract
Lavandula Stoechas Extract
Sodium Cocamidopropyl Betaine
Sodium Cocoyl Isethionate
Sodium Hydroxide
Sodium Laureth Sulfate
Waters